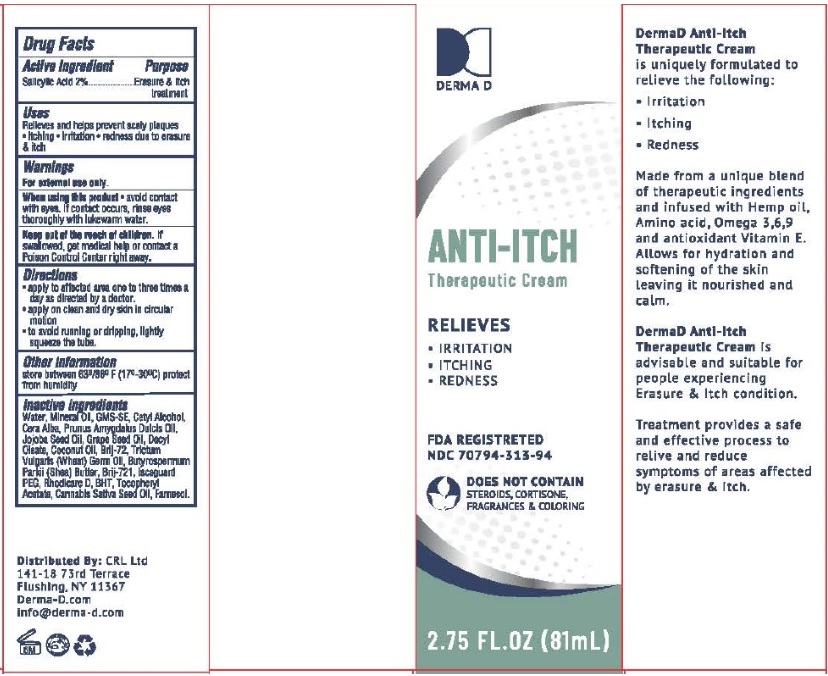 DRUG LABEL: DermaD ANTI-ITCH Therapeutic
NDC: 70794-313 | Form: CREAM
Manufacturer: Chen Cohen Industries Inc.
Category: otc | Type: HUMAN OTC DRUG LABEL
Date: 20250529

ACTIVE INGREDIENTS: SALICYLIC ACID 20 mg/1 g
INACTIVE INGREDIENTS: WATER; MINERAL OIL; GLYCERYL MONOSTEARATE; CETYL ALCOHOL; WHITE WAX; ALMOND OIL; JOJOBA OIL; GRAPE SEED OIL; DECYL OLEATE; COCONUT OIL; WHEAT GERM OIL; STEARETH-2; STEARETH-21; SHEA BUTTER; .ALPHA.-TOCOPHEROL; BUTYLATED HYDROXYTOLUENE; FARNESOL; CANNABIS SATIVA SEED OIL

Drug Facts

Active Ingredient

Salicylic Acid....2%

Purpose

Erasure & Itch treatment

Uses

Relieves and helps prevent scaly plaques

- itching
- irritation
- redness and flaking due to erasure & itch

Warnings

For external use only

When using this product

avoid contact with eyes. If contact occurs, rinse eyes thoroughly with lukewarm water.

Keep out of reach of children

If swallowed, get medical help or contact a Poison Control Center right away.

Directions

- Apply to the affected area one to three times a day or as directed by a doctor.
- Apply on clean and dry skin in circular motion.
- To avoid running or dripping, lightly squeeze the tube.

Other Information

Store between 63°/80°F (17-30C)

Protect from humidity.

Inactive Ingredients

water, mineral oil, GMS-SE, cetyl alcohol, Cera Alba, Prunus Amygdalus Dulcis Oil, Jojoba Seed Oil, Grape Seed Oil, Decyl Oleate, coconut oil, Brij-72, Trictum Vulgaris (wheat) germ oil, Butyrospermum Parkii (shea) butter, Brij-721, Iscaguard PEG, Rhodicare D, Tocopheryl Acetate, Cannabis Sativa Oil, B.H.T, farnesol

Principal Display Panel

NDC 70794-313-94

DERMAD PSORIASIS Therapeutic Cream

RELIEVES

- IRRITATION
- ITCHING
- REDNESS
- SCALING

FDA REGISTERED

DOES NOT CONTAIN STEROIDS, CORTISONE, FRAGRANCES AND COLORINGS

2.75 FL. OZ (81 mL)